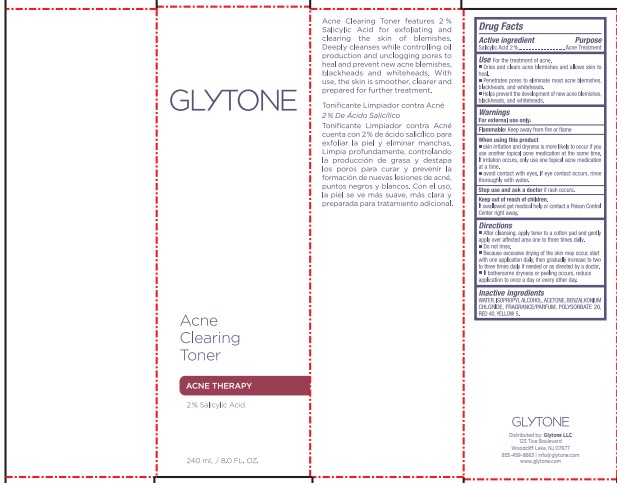 DRUG LABEL: Acne Clearing Toner
NDC: 84262-011 | Form: LIQUID
Manufacturer: GLYTONE LLC
Category: otc | Type: HUMAN OTC DRUG LABEL
Date: 20240628

ACTIVE INGREDIENTS: SALICYLIC ACID 2 mg/1 mL
INACTIVE INGREDIENTS: CALENDULA OFFICINALIS FLOWER; ICODEXTRIN; GLYCERIN; LEUCONOSTOC/RADISH ROOT FERMENT FILTRATE; 1,2-HEXANEDIOL; CAPRYLYL GLYCOL; APPLE; CITRIC ACID MONOHYDRATE; SAW PALMETTO; AMYLOPECTIN, UNSPECIFIED SOURCE; MANDELIC ACID; POLYSORBATE 20; SODIUM HYDROXIDE; POLYDEXTROSE; EPILOBIUM FLEISCHERI WHOLE; GLYCYRRHIZA GLABRA; SODIUM BENZOATE; PROPANEDIOL; HAMAMELIS VIRGINIANA TOP; NIACINAMIDE; ALLANTOIN; POTASSIUM SORBATE; SALIX ALBA BARK; ALOE VERA LEAF

Glytone Acne Clearing Toner

Active Ingredient

Salicylic Acid 2%

Purpose

Acne Treatment

Use

For the treatment of acne.

- Dries and clears acne blemishes and allows skin to heal.
- Penetrates pores to eliminate most acne blemishes, blackheads, and whiteheads.
- Helps prevent the development of new acne blemishes, blackheads, and whiteheads.

Warnings

For external use only.

Flammable

Keep away from fire or flame

When using this product

- skin irritation and dryness is more likely to occur if you use another topical acne medication at the same time. If irritation occurs, only use one topical acne medication at a time.
- avoid contact with eyes. If eye contact occurs, rinse thoroughly with water.

Stop use and ask a doctor

if rash occurs.

Keep out of reach of children.

If swallowed get medical help or contact a Poison Control Center right away.

Directions

- After cleansing, apply toner to a cotton pad and gently apply over affected area one to three times daily.
- Do not rinse.
- Because excessive drying of the skin may occur, start with one application daily, then gradually increase to two to three times daily if needed or as directed by a doctor.
- If bothersome dryness or peeling occurs, reduce application to once a day or every toher day.

Inactive Ingredients

WATER, ISOPROPRYL ALCOHOL, ACETONE, BENZALKONIUM CHLORIDE, FRAGRANCE/PARFUM, POLYSORBATE 20, RED 40, YELLOW 5

PACKAGE LABEL

GLYTONE

ACNE CLEARING TONER

ACNE THERAPY

2% SALICYLIC ACID

240 mL / 8.0 FL. OZ.